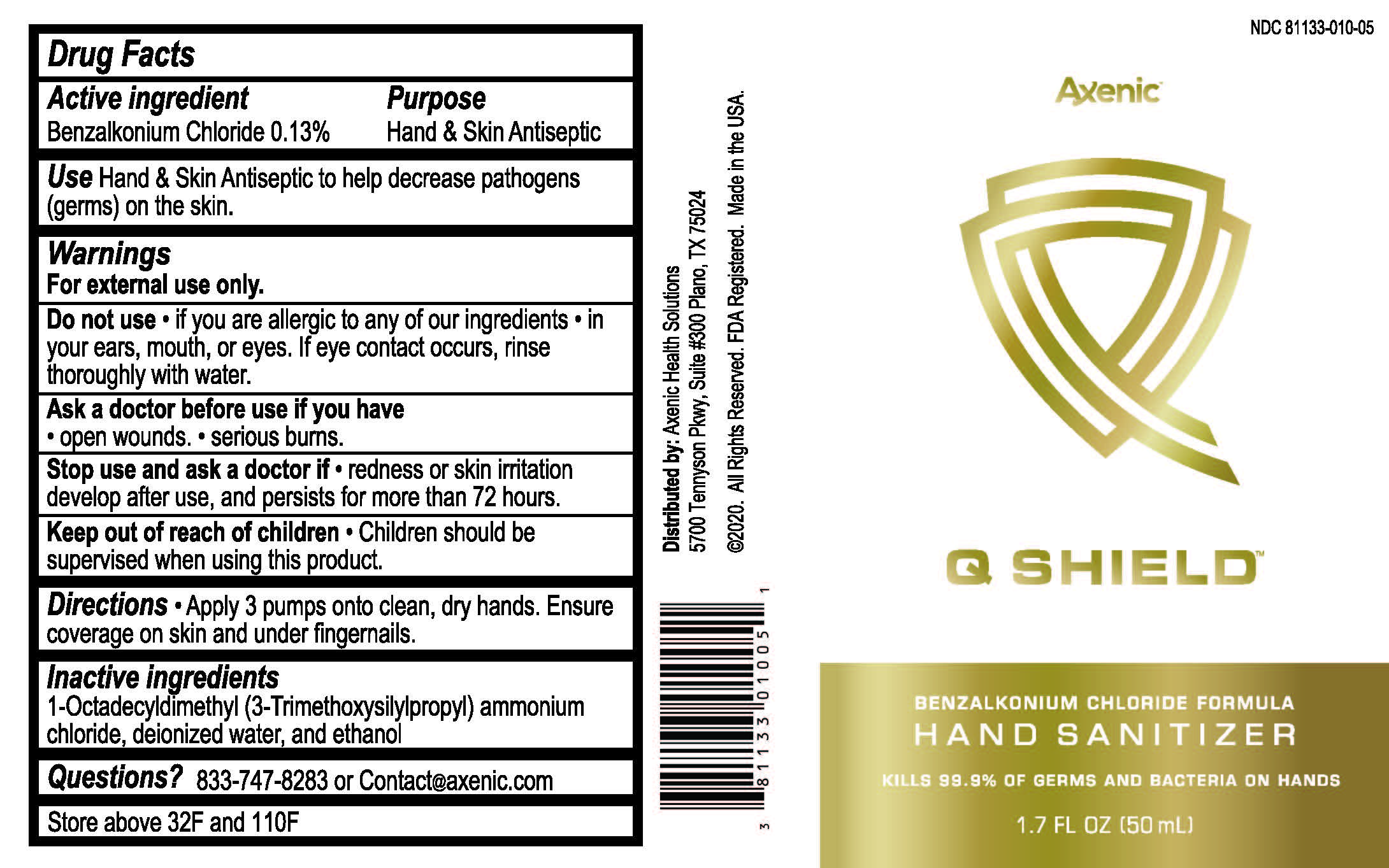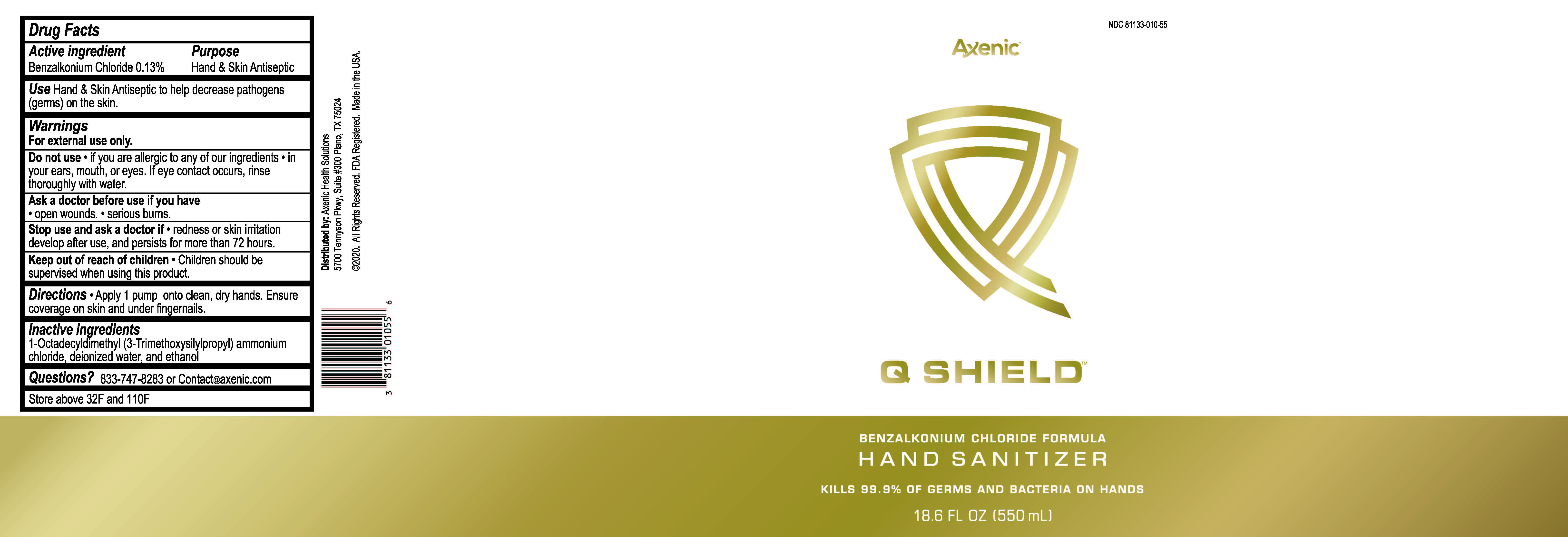 DRUG LABEL: Q Shield Hand
NDC: 81133-010 | Form: LIQUID
Manufacturer: Axenic Health Solutions, Inc.
Category: otc | Type: HUMAN OTC DRUG LABEL
Date: 20201222

ACTIVE INGREDIENTS: BENZALKONIUM CHLORIDE 0.13 g/100 mL
INACTIVE INGREDIENTS: DIMETHYLOCTADECYL(3-(TRIMETHOXYSILYL)PROPYL)AMMONIUM CHLORIDE; ALCOHOL; WATER

Drug Facts

ACTIVE INGREDIENT

Benzalkonium Chloride 0.13%

PURPOSE

Hand and skin Antiseptic

INDICATIONS AND USAGE

Hand and Skin Antiseptic to help decrease pathogens (germs) on the skin

WARNINGS

For external use only

DO NOT USE

* If you are allergic to any of our ingredients

* In you ears, mouth, or eyes

* If eye contact occurs, rinse thoroughly with water

ASK DOCTOR

Open wounds

Serious burns

STOP USE

Redness or skin irritation develop after use, and persists for more than 72 hours.

Children should be supervised when using this product.

DOSAGE AND ADMINISTRATION

Apply 3 pumps onto clean, dry hands. Ensure covergae on skin and under fingernails.

INACTIVE INGREDIENT

1-Octadecyldimethyl (3-Trimethoxysilylpropyl) ammonium chloride, deionized water, and ethanol

QUESTIONS

Call: 833-747-8283 or e-mail: contact@axenic.com

PACKAGE LABEL

Axenic Q Shield

Benzalkonium Chloride Formula

Hand Sanitizer

Kills 99.9% of Germs and Bacteria on Hands

Distributed by:

Axenic Health Solutions

5700 Terryson Pkwy, Suite #300 Plano, TX 75024

(C)2020. All rrights Researved.

FDA Registered.

Made in the USA

NDC: 81133-010-XX